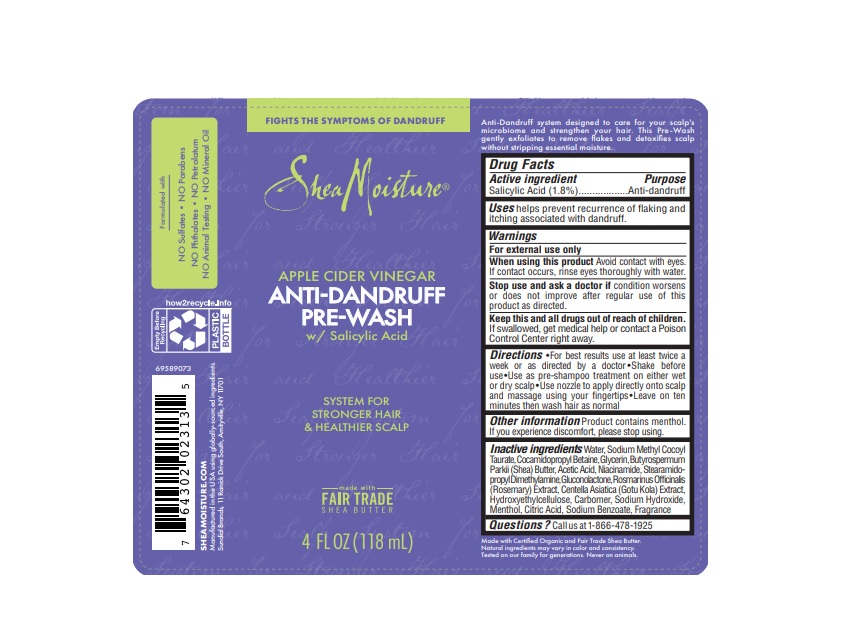 DRUG LABEL: Shea Moisture
NDC: 64942-2084 | Form: LIQUID
Manufacturer: Conopco, Inc. d/b/a/ Unilever
Category: otc | Type: HUMAN OTC DRUG LABEL
Date: 20241107

ACTIVE INGREDIENTS: SALICYLIC ACID 1.8 g/100 mL
INACTIVE INGREDIENTS: CITRIC ACID MONOHYDRATE; SODIUM BENZOATE; SODIUM HYDROXIDE; WATER; COCAMIDOPROPYL BETAINE; SODIUM METHYL COCOYL TAURATE; GLYCERIN; SHEA BUTTER; GLUCONOLACTONE; ROSEMARY; ACETIC ACID; NIACINAMIDE; STEARAMIDOPROPYL DIMETHYLAMINE; MENTHOL; CARBOMER HOMOPOLYMER, UNSPECIFIED TYPE; HYDROXYETHYL CELLULOSE, UNSPECIFIED

Shea Moisture Apple Cider Vinegar Anti-dandruff Pre-Wash

Drug Facts

Active ingredient

Salicylic Acid (1.8%)

Purpose

Anti-dandruff

Uses

helps prevent recurrence of flaking and itching associated with dandruff.

Warnings

For external use only
When using this product avoid contact with eyes. If contact occurs, rinse eyes thoroughtly with water.
Stop use and ask a doctor if condition worsens or does not improve after regular use of this product as directed.

KEEP OUT OF REACH OF CHILDREN

Keep this and all drugs out of reach of children.
If swallowed, get medical help or contact a Poison Control Center right away.

Directions

For best results use at least twice a week or as directed by doctor. Shake well before use. Use as pre-shampoo treatment on either wet or dry scalp. Use nozzle to apply directly onto scalp and massage using your fingertips. Leave on ten minutes then wash hair as normal.

Other information

Product contains menthol. If you experience discomfort, please stop using.

Inactive Ingredients

Water, Sodium Methyl Cocoyl Taurate, Cocamidopropyl Betaine, Glycerin, Butyrospermum Parkii (Shea) Butter, Acetic Acid, Niacinamide, Stearamidopropyl Dimethylamine, Gluconolactone, Rosmarinus Officinalis (Rosemary) Extract, Centella Asiatica (Gotu Kola) Extract, Hydroxyethylcellulose, Carbomer, Sodium Hydroxide, Menthol, Citric Acid, Sodium Benzoate, Fragrance

Questions?

Call us at 1-866-478-1925